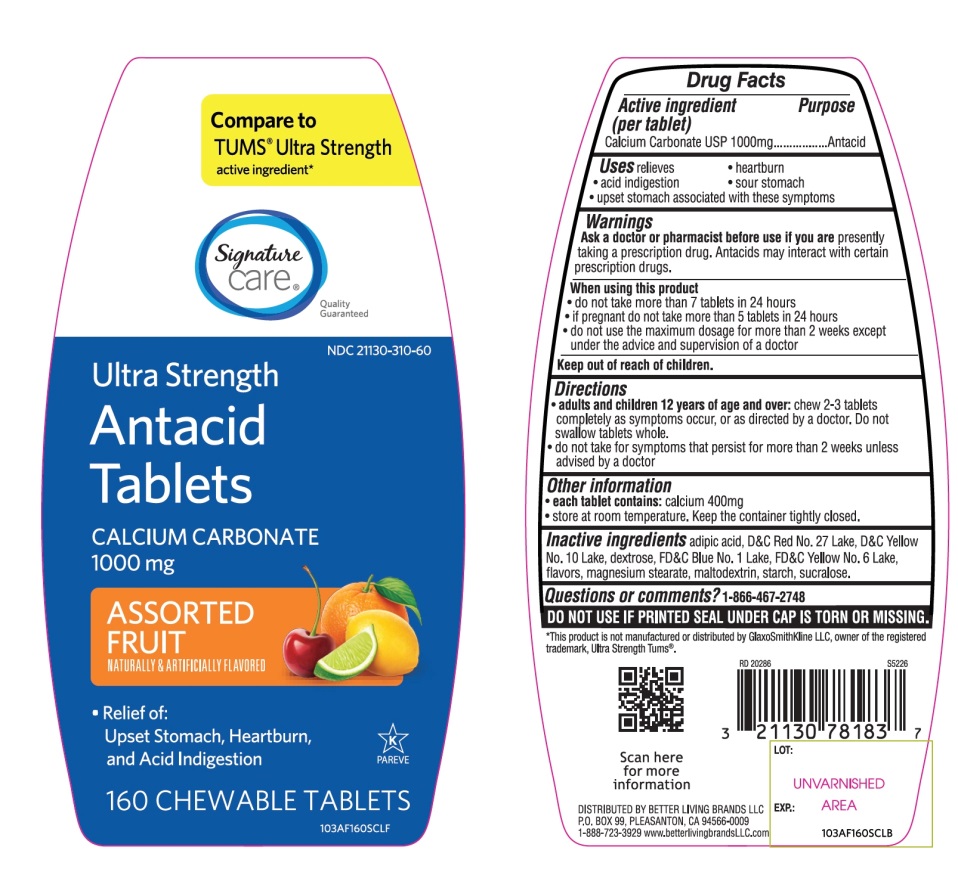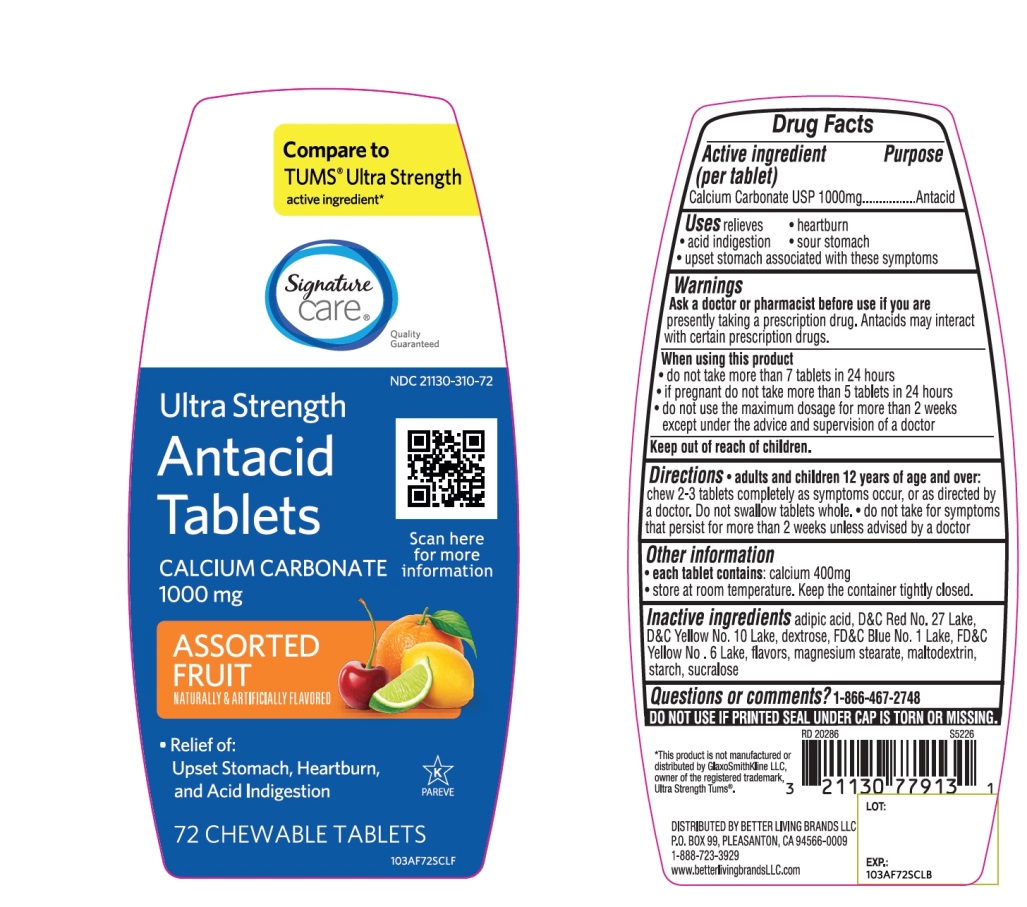 DRUG LABEL: Ultra Strength
NDC: 21130-310 | Form: TABLET, CHEWABLE
Manufacturer: BETTER LIVING BRANDS LLC
Category: otc | Type: HUMAN OTC DRUG LABEL
Date: 20251029

ACTIVE INGREDIENTS: CALCIUM CARBONATE 1000 mg/1 1
INACTIVE INGREDIENTS: ADIPIC ACID; D&C RED NO. 27; D&C YELLOW NO. 10; DEXTROSE, UNSPECIFIED FORM; FD&C BLUE NO. 1; FD&C YELLOW NO. 6; MAGNESIUM STEARATE; MALTODEXTRIN; STARCH, CORN; SUCRALOSE

Ultra Strength Assorted fruits Flavor Chewable Tablets

Active ingredient (per tablet)

Calcium Carbonate USP 1,000mg

Purpose

Antacid

Uses

relieves

- heartburn
- sour stomach
- acid indigestion
- upset stomach associated with these symptoms

Warnings

Ask a doctor or pharmacist before use if you are presentlytaking a prescription drug. Antacids may interact with certain prescription drugs.

When using this product

- do not take more than 7 tablets in 24 hours
- if pregnant do not take more than 5 tablets in 24 hours
- do not use the maximum dosage for more than 2 weeks except under the advice and supervision of a doctor.

Directions

- adults and children 12 years of age and over:chew 2-3 tablets as symptoms occur, or as directed by a doctor
- do not take for symptoms that persist for more than 2 weeks unless advised by a doctor

Other information

- each tablet contains:elemental calcium 400mg
- store at room temperature. Keep the container tightly closed

Inactive ingredients

adipic acid, D&C Red No. 27 Lake, D&C Yellow No.10 Lake, dextrose, FD&C Blue No. 1 Lake, FD&C Yellow No. 6, flavor, magnesium stearate, maltodextrin, starch, sucralose.

Questions or comments?

1-866-467-2748

SAFETY SEALED: DO NOT USE IF PRINTED SEAL UNDER CAP IS TORN OR MISSING

Package/Label Principal Display Panel

* Compare to the active ingredients in Ultra Strength Tums®

ULTRA STRENGTH

Antacid Tablets

Calcium Carbonate 1000mg

Relieves of:

- Acid indigestion
- Sour Stomach
- Heartburn

Assorted Fruit Flavors

GLUTEN-FREE

Distributed by:

*This product is not manufactured and distributed by GlaxoSmithKline LLC, owner of the registered trademark, Ultra Strength Tums®

Package Label 160 Chewable Tablets